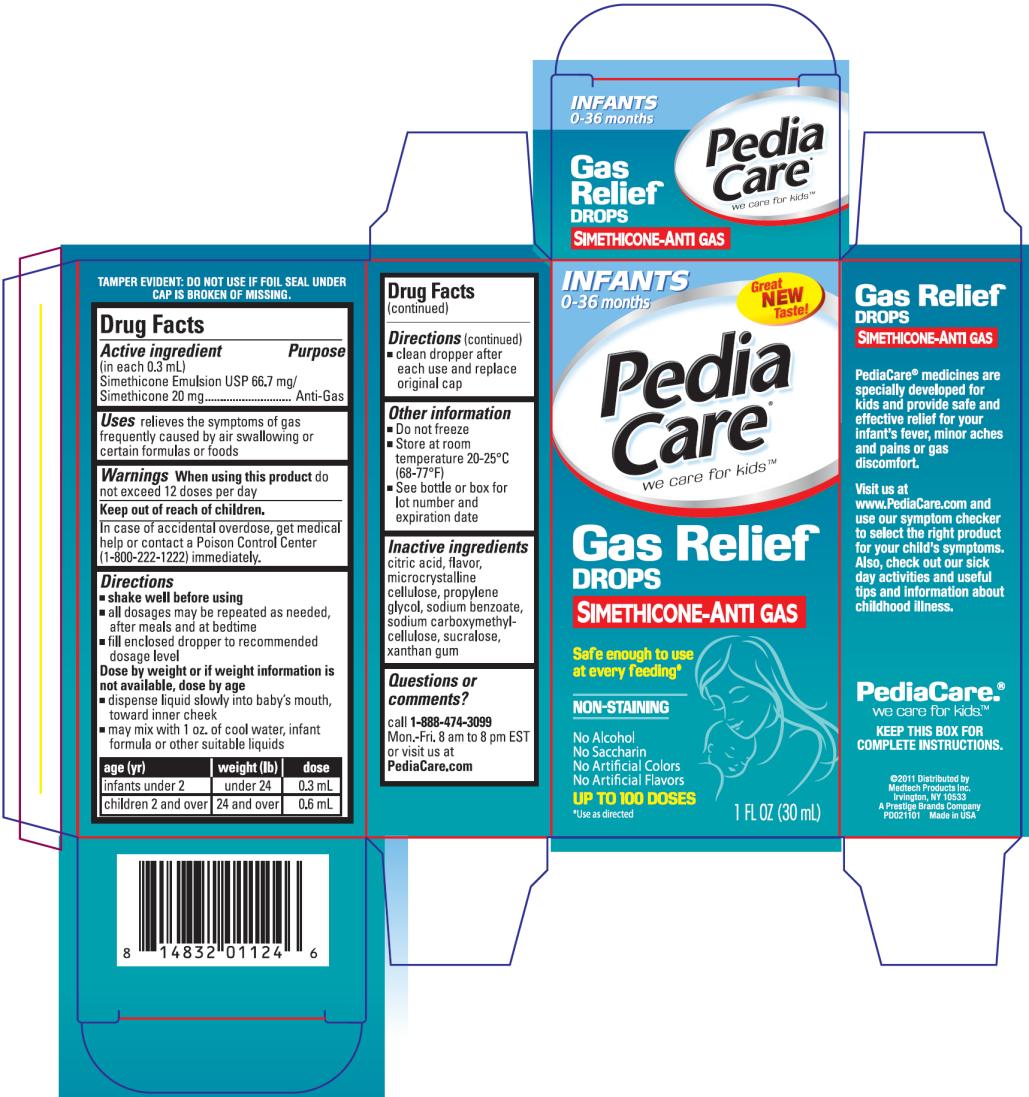 DRUG LABEL: PediaCare Gas Relief Drops Dye Free
NDC: 63029-811 | Form: LIQUID
Manufacturer: Medtech Products Inc.
Category: otc | Type: HUMAN OTC DRUG LABEL
Date: 20120413

ACTIVE INGREDIENTS: SILICON DIOXIDE 0.011 g/1 mL; DIMETHICONE 0.211 g/1 mL
INACTIVE INGREDIENTS: CITRIC ACID MONOHYDRATE; CELLULOSE, MICROCRYSTALLINE; PROPYLENE GLYCOL; SODIUM BENZOATE; CARBOXYMETHYLCELLULOSE SODIUM; SUCRALOSE; XANTHAN GUM

PediaCare Gas Relief Drops Dye Free

Drug Facts

Active ingredient

(in each 0.3 mL)

Simethicone Emulsion USP 66.7mg/Simethicone 20 mg

Purpose

Anti-Gas

Uses

relieves the symptoms of gas frequently caused by air swallowing or certain formulas or foods

Warnings

When using this product

do not exceed 12 doses per day

Keep out of reach of children.

In case of accidental overdose, get medical help or contact a Poison Control Center (1-800-222-1222) immediately.

Directions

- shake well before using
- all dosages may be repeated as needed, after meals and at bedtime
- fill enclosed dropper to recommended dosage level

Dose by weight or if weight information is not available, dose by age.

- dispense liquid slowly into baby’s mouth, toward inner cheek
- may mix with 1 oz. of cool water, infant formula or other suitable liquids
- clean dropper after each use and replace original cap

age (yr) | weight (lb) | dose
infants under 2 | under 24 | 0.3 mL
children 2 and over | 24 and over | 0.6 mL

Other information

- Do not freeze
- Store at room temperature 20-25ºC (68-77ºF)
- See bottle or box for lot number and expiration date

Inactive ingredients

citric acid, flavor, microcrystalline cellulose, propylene glycol, sodium benzoate, sodium carboxymethylcellulose, sucralose, xanthan gum

Questions or comments?

call 1-888-474-3099 Mon. – Fri. 8 am to 8 pm EST or visit us at PediaCare.com

PRINCIPAL DISPLAY PANEL

INFANTS 0-36 months
PediaCare® we care for kidsTM
Gas Relief DROPS
SIMETHICONE-ANTI GAS
NON-STAINING
1 FL OZ (30 mL)